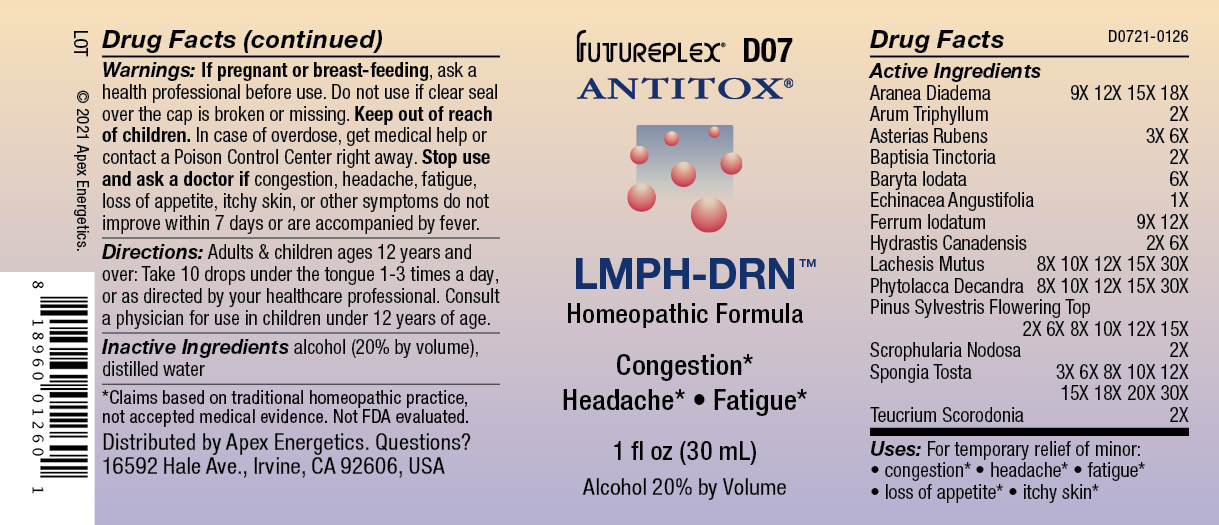 DRUG LABEL: D07
NDC: 63479-0407 | Form: SOLUTION
Manufacturer: Apex Energetics Inc.
Category: homeopathic | Type: HUMAN OTC DRUG LABEL
Date: 20240108

ACTIVE INGREDIENTS: ARANEUS DIADEMATUS 18 [hp_X]/1 mL; ARISAEMA TRIPHYLLUM ROOT 2 [hp_X]/1 mL; ASTERIAS RUBENS 6 [hp_X]/1 mL; BAPTISIA TINCTORIA ROOT 2 [hp_X]/1 mL; BARIUM IODIDE 6 [hp_X]/1 mL; ECHINACEA ANGUSTIFOLIA 1 [hp_X]/1 mL; FERROUS IODIDE 12 [hp_X]/1 mL; GOLDENSEAL 6 [hp_X]/1 mL; LACHESIS MUTA VENOM 30 [hp_X]/1 mL; PHYTOLACCA AMERICANA ROOT 30 [hp_X]/1 mL; PINUS SYLVESTRIS FLOWERING TOP 15 [hp_X]/1 mL; SCROPHULARIA NODOSA 2 [hp_X]/1 mL; SPONGIA OFFICINALIS SKELETON, ROASTED 30 [hp_X]/1 mL; TEUCRIUM SCORODONIA FLOWERING TOP 2 [hp_X]/1 mL
INACTIVE INGREDIENTS: WATER; ALCOHOL

D07

Active Ingredients
Aranea Diadema | 9X 12X 15X 18X
Arum Triphyllum | 2X
Asterias Rubens | 3X 6X
Baptisia Tinctoria | 2X
Baryta Iodata | 6X
Echinacea Angustifolia | 1X
Ferrum Iodatum | 9X 12X
Hydrastis Canadensis | 2X 6X
Lachesis Mutus | 8X 10X 12X 15X 30X
Phytolacca Decandra | 8X 10X 12X 15X 30X
Pinus Sylvestris Flowering Top | 2X 6X 8X 10X 12X 15X
Scrophularia Nodosa | 2X
Spongia Tosta | 3X 6X 8X 10X 12X 15X 18X 20X 30X
Teucrium Scorodonia | 2X

INDICATIONS AND USAGE

For temporary relief of minor:

congestion*

headache*

fatigue*

loss of appetite*

itchy skin*

*Claims based on traditional homeopathic practice, not accepted medical evidence. Not FDA evaluated.

Uses:

For temporary relief of minor:

congestion*

headache*

fatigue*
loss of appetite*

itchy skin*

*Claims based on traditional homeopathic practice, not accepted medical evidence. Not FDA evaluated.

Warnings:

PREGNANCY OR BREAST FEEDING

If pregnant or breast-feeding, ask a health professional before use.

Do not use if clear seal over the cap is broken or missing.

Keep out of reach of children. In case of overdose, get medical help or contact a Poison Control Center right away.

Stop use and ask a doctor if congestion, headache, fatigue, loss of appetite, itchy skin, or other symptoms do not improve within 7 days or are accompanied by fever.

Directions:

Adults & children ages 12 years and over: Take 10 drops under the tongue 1-3 times a day, or as directed by your healthcare professional. Consult a physician for use in children under 12 years of age.

Inactive Ingredients

alcohol (20% by volume), distilled water

Distributed by Apex Energetics. Questions?
16592 Hale Ave., Irvine, CA 92606, USA

PACKAGE LABEL

FUTUREPLEX® D07

ANTITOX®

LMPH-DRN™

Homeopathic Formula

Congestion
Headache • Fatigue

1 fl oz (30 mL)

Alcohol 20% by Volume